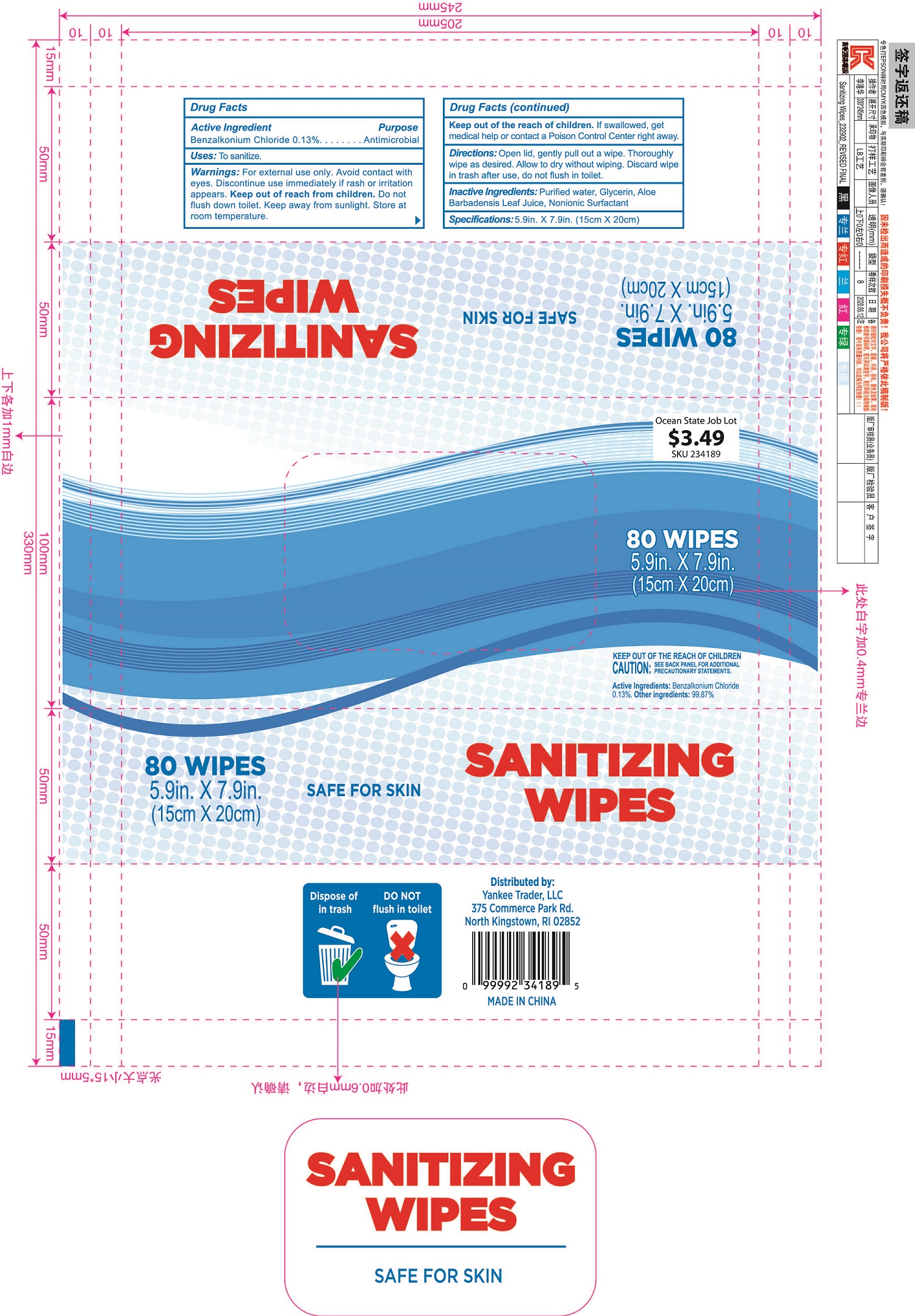 DRUG LABEL: Sanitising Wipes
NDC: 69821-004 | Form: CLOTH
Manufacturer: Zhejiang Qimei Commodity Co.,Ltd.
Category: otc | Type: HUMAN OTC DRUG LABEL
Date: 20221121

ACTIVE INGREDIENTS: BENZALKONIUM CHLORIDE 0.13 g/100 g
INACTIVE INGREDIENTS: WATER; GLYCERIN; ALOE VERA LEAF; POLYSORBATE 20

69821-004 0.13% Benzalkonium Chloride Sanitising Wipes

Active ingredient

benzalkonium chloride 0.13%

Purpose

Antibacterial

Uses

To sanitize.

Warnings

Warnings: For external use only, Avoid contact with
eyes. Discontinue use immediately if rash or irritation
appears. Keep out of reach from children. Do not
flush down toilet. Keep away from sunlight. Store at
room temperature.

keep out of reach of children .if swallowed, get medical help or contact a Poison Control Center right away.

Directions

Directions: Open lid, gently pull out a wipe. Thoroughly
wipe as desired. Allow to dry without wiping. Discard wipe
in trash after use, do not flush in toilet.

INACTIVE INGREDIENT

Purified water, Glycerin, Aloe Barbadensis Leaf Juice, Nonionic Surfactant